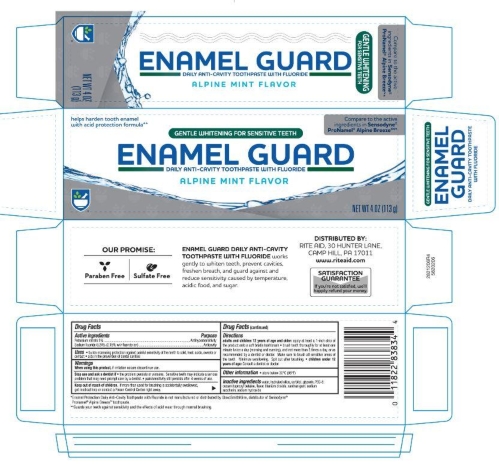 DRUG LABEL: Rite Aid
NDC: 11822-6020 | Form: PASTE, DENTIFRICE
Manufacturer: Rite Aid
Category: otc | Type: HUMAN OTC DRUG LABEL
Date: 20251121

ACTIVE INGREDIENTS: SODIUM FLUORIDE 0.15 g/100 g; POTASSIUM NITRITE 5 g/100 g
INACTIVE INGREDIENTS: GLYCERIN; SACCHARIN SODIUM; WATER; SODIUM HYDROXIDE; XANTHAN GUM; COCAMIDOPROPYL BETAINE; POLYETHYLENE GLYCOL, UNSPECIFIED; HYDRATED SILICA; SORBITOL; TITANIUM DIOXIDE

5820206 Rite Aid Enamel Guard (8015164)

Drug Facts

Active ingredients

Potassium nitrate 5%

Sodium fluoride 0.15% w/v fluoride ion

Purpose

Antihypersensitivity

Anticavity

Uses

- aids in the prevention of dental caviites
- aids in reducing sensitivity

Warnings

If pain/sensitivity persists after 4 weeks of use, please visit your dentist.

Stop use and see your doctor if the problem worsens. Sensitive teeth may indicate a serious problem that may need prompt care by a dentist.

Keep out of reach of children. If more than used for brushing is accidentally swallowed, get medical help or contact a Poison Control Center right away.

Directions

Adults and children 12 years of age and older: Apply at least a 1-inch strip of the product onto a soft bristle toothbruch.

- Brush teeth thorughly for at least one minute, preferably after each meal or at least twice a day (morning and evening) or as directed by a dentist or physician. Make sure to brush all sensitive areas of the teeth.
- Children under 12 years of age: consult a dentist or doctor.

INACTIVE INGREDIENT

Inactive ingredients water, hydrated silica, sorbitol, glycerin, PEG-8, cocamidpropyl betaine, flavor, titanium dioxide, xanthan gum, sodium saccharin, sodium hydroxide

STORAGE AND HANDLING

Store in a cool, dry place.

DISTRIBUTED BY:

RITE AID, 30 HUNTER LANE

CAMP HILL, PA 17011

MADE IN USA